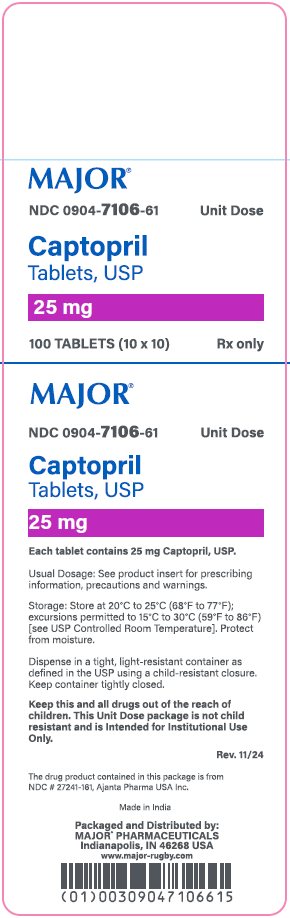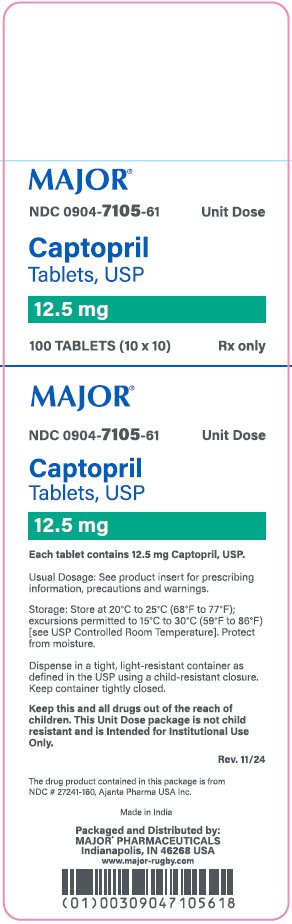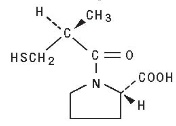 DRUG LABEL: Captopril
NDC: 0904-7105 | Form: TABLET
Manufacturer: Major Pharmaceuticals
Category: prescription | Type: HUMAN PRESCRIPTION DRUG LABEL
Date: 20260123

ACTIVE INGREDIENTS: CAPTOPRIL 12.5 mg/1 1
INACTIVE INGREDIENTS: MICROCRYSTALLINE CELLULOSE; ANHYDROUS LACTOSE; CROSPOVIDONE, UNSPECIFIED; SILICON DIOXIDE; STEARIC ACID

Captopril Tablets, USP
Rx only

WARNING: FETAL TOXICITY

- When pregnancy is detected, discontinue captopril tablets as soon as possible.
- Drugs that act directly on the renin-angiotensin system can cause injury and death to the developing fetus. See WARNINGS: Fetal Toxicity

DESCRIPTION

Captopril tablets, USP are a specific competitive inhibitor of angiotensin I-converting enzyme (ACE), the enzyme responsible for the conversion of angiotensin I to angiotensin II.

Captopril is designated chemically as 1-[(2S)-3-mercapto-2-methylpropionyl] -L-proline [MW 217.28] and has the following structure:

Captopril USP is a white to off-white crystalline powder that may have a slight sulfurous odor; it is soluble in water (approx. 126 mg/mL), methanol, and ethanol and sparingly soluble in chloroform and ethyl acetate.

Captopril tablets, USP are available in potencies of 12.5 mg, 25 mg, 50 mg, and 100 mg as scored tablets for oral administration.

Inactive ingredients: microcrystalline cellulose, lactose, crospovidone, colloidal silicon dioxide and stearic acid.

CLINICAL PHARMACOLOGY

Mechanism of Action

The mechanism of action of captopril has not yet been fully elucidated. Its beneficial effects in hypertension and heart failure appear to result primarily from suppression of the renin-angiotensin-aldosterone system. However, there is no consistent correlation between renin levels and response to the drug. Renin, an enzyme synthesized by the kidneys, is released into the circulation where it acts on a plasma globulin substrate to produce angiotensin I, a relatively inactive decapeptide. Angiotensin I is then converted by angiotensin converting enzyme (ACE) to angiotensin II, a potent endogenous vasoconstrictor substance. Angiotensin II also stimulates aldosterone secretion from the adrenal cortex, thereby contributing to sodium and fluid retention.

Captopril prevents the conversion of angiotensin I to angiotensin II by inhibition of ACE, a peptidyldipeptide carboxy hydrolase. This inhibition has been demonstrated in both healthy human subjects and in animals by showing that the elevation of blood pressure caused by exogenously administered angiotensin I was attenuated or abolished by captopril. In animal studies, captopril did not alter the pressor responses to a number of other agents, including angiotensin II and norepinephrine, indicating specificity of action.

ACE is identical to ''bradykininase'', and captopril may also interfere with the degradation of the vasodepressor peptide, bradykinin. Increased concentrations of bradykinin or prostaglandin E2 may also have a role in the therapeutic effect of captopril.

Inhibition of ACE results in decreased plasma angiotensin II and increased plasma renin activity (PRA), the latter resulting from loss of negative feedback on renin release caused by reduction in angiotensin II. The reduction of angiotensin II leads to decreased aldosterone secretion, and, as a result, small increases in serum potassium may occur along with sodium and fluid loss.

The antihypertensive effects persist for a longer period of time than does demonstrable inhibition of circulating ACE. It is not known whether the ACE present in vascular endothelium is inhibited longer than the ACE in circulating blood.

Pharmacokinetics

After oral administration of therapeutic doses of captopril, rapid absorption occurs with peak blood levels at about one hour. The presence of food in the gastrointestinal tract reduces absorption by about 30 percent to 40 percent; captopril therefore should be given one hour before meals. Based on carbon-14 labeling, average minimal absorption is approximately 75 percent. In a 24-hour period, over 95 percent of the absorbed dose is eliminated in the urine; 40 percent to 50 percent is unchanged drug; most of the remainder is the disulfide dimer of captopril and captopril-cysteine disulfide.

Approximately 25 percent to 30 percent of the circulating drug is bound to plasma proteins. The apparent elimination half-life for total radioactivity in blood is probably less than 3 hours. An accurate determination of half-life of unchanged captopril is not, at present, possible, but it is probably less than 2 hours. In patients with renal impairment, however, retention of captopril occurs (see DOSAGE AND ADMINISTRATION).

Pharmacodynamics

Administration of captopril results in a reduction of peripheral arterial resistance in hypertensive patients with either no change, or an increase, in cardiac output. There is an increase in renal blood flow following administration of captopril and glomerular filtration rate is usually unchanged.

Reductions of blood pressure are usually maximal 60 minutes to 90 minutes after oral administration of an individual dose of captopril. The duration of effect is dose related. The reduction in blood pressure may be progressive, so to achieve maximal therapeutic effects, several weeks of therapy may be required. The blood pressure lowering effects of captopril and thiazide-type diuretics are additive. In contrast, captopril and beta-blockers have a less than additive effect.

Blood pressure is lowered to about the same extent in both standing and supine positions. Orthostatic effects and tachycardia are infrequent but may occur in volume-depleted patients. Abrupt withdrawal of captopril has not been associated with a rapid increase in blood pressure.

In patients with heart failure, significantly decreased peripheral (systemic vascular) resistance and blood pressure (afterload), reduced pulmonary capillary wedge pressure (preload) and pulmonary vascular resistance, increased cardiac output, and increased exercise tolerance time (ETT) have been demonstrated. These hemodynamic and clinical effects occur after the first dose and appear to persist for the duration of therapy. Placebo controlled studies of 12 weeks duration in patients who did not respond adequately to diuretics and digitalis show no tolerance to beneficial effects on ETT; open studies, with exposure up to 18 months in some cases, also indicate that ETT benefit is maintained. Clinical improvement has been observed in some patients where acute hemodynamic effects were minimal.

The Survival and Ventricular Enlargement (SAVE) study was a multicenter, randomized, double-blind, placebo-controlled trial conducted in 2,231 patients (age 21 years to 79 years) who survived the acute phase of myocardial infarction and did not have active ischemia. Patients had left ventricular dysfunction (LVD), defined as a resting left ventricular ejection fraction ≤ 40%, but at the time of randomization were not sufficiently symptomatic to require ACE inhibitor therapy for heart failure. About half of the patients had symptoms of heart failure in the past. Patients were given a test dose of 6.25 mg oral captopril tablets and were randomized within 3 days to 16 days post-infarction to receive either captopril or placebo in addition to conventional therapy. Captopril tablets were initiated at 6.25 mg or 12.5 mg three times a day and after two weeks titrated to a target maintenance dose of 50 mg three times a day. About 80% of patients were receiving the target dose at the end of the study. Patients were followed for a minimum of two years and for up to five years, with an average follow-up of 3.5 years.

Baseline blood pressure was 113/70 mmHg and 112/70 mmHg for the placebo and captopril groups, respectively. Blood pressure increased slightly in both treatment groups during the study and was somewhat lower in the captopril group (119/74 mmHg vs. 125/77 mmHg at 1 yr).

Therapy with captopril improved long-term survival and clinical outcomes compared to placebo. The risk reduction for all cause mortality was 19% (P = 0.02) and for cardiovascular death was 21% (P = 0.014). Captopril treated subjects had 22% (P = 0.034) fewer first hospitalizations for heart failure. Compared to placebo, 22% fewer patients receiving captopril developed symptoms of overt heart failure. There was no significant difference between groups in total hospitalizations for all cause (2,056 placebo; 2,036 captopril).

Captopril was well tolerated in the presence of other therapies such as aspirin, beta blockers, nitrates, vasodilators, calcium antagonists and diuretics.

In a multicenter, double-blind, placebo controlled trial, 409 patients, age 18 to 49 of either gender, with or without hypertension, with type I (juvenile type, onset before age 30) insulin-dependent diabetes mellitus, retinopathy, proteinuria ≥ 500 mg per day and serum creatinine ≤ 2.5 mg/dL, were randomized to placebo or captopril tablets (25 mg three times a day) and followed for up to 4.8 years (median 3 years). To achieve blood pressure control, additional antihypertensive agents (diuretics, beta blockers, centrally acting agents or vasodilators) were added as needed for patients in both groups.

The captopril group had a 51% reduction in risk of doubling of serum creatinine (P < 0.01) and a 51% reduction in risk for the combined endpoint of end-stage renal disease (dialysis or transplantation) or death (P < 0.01). Captopril treatment resulted in a 30% reduction in urine protein excretion within the first 3 months (P < 0.05), which was maintained throughout the trial. The captopril group had somewhat better blood pressure control than the placebo group, but the effects of captopril on renal function were greater than would be expected from the group differences in blood pressure reduction alone. Captopril was well tolerated in this patient population.

In two multicenter, double-blind, placebo controlled studies, a total of 235 normotensive patients with insulin-dependent diabetes mellitus, retinopathy and microalbuminuria (20 mcg/min to 200 mcg/min) were randomized to placebo or captopril tablets (50 mg twice daily) and followed for up to 2 years. Captopril delayed the progression to overt nephropathy (proteinuria ≥ 500 mg/day) in both studies (risk reduction 67% to 76%; P < 0.05). Captopril also reduced the albumin excretion rate. However, the long term clinical benefit of reducing the progression from microalbuminuria to proteinuria has not been established.

Studies in rats and cats indicate that captopril does not cross the blood-brain barrier to any significant extent.

INDICATIONS AND USAGE

Hypertension: Captopril tablets, USP, are indicated for the treatment of hypertension.

In using captopril tablets, USP, consideration should be given to the risk of neutropenia/agranulocytosis (see WARNINGS).

Captopril tablets, USP may be used as initial therapy for patients with normal renal function, in whom the risk is relatively low. In patients with impaired renal function, particularly those with collagen vascular disease, captopril should be reserved for hypertensives who have either developed unacceptable side effects on other drugs, or have failed to respond satisfactorily to drug combinations.

Captopril tablets, USP are effective alone and in combination with other antihypertensive agents, especially thiazidetype diuretics. The blood pressure lowering effects of captopril and thiazides are approximately additive.

Heart Failure: Captopril tablets, USP are indicated in the treatment of congestive heart failure usually in combination with diuretics and digitalis. The beneficial effect of captopril in heart failure does not require the presence of digitalis, however, most controlled clinical trial experience with captopril has been in patients receiving digitalis, as well as diuretic treatment.

Left Ventricular Dysfunction After Myocardial Infarction: Captopril tablets, USP are indicated to improve survival following myocardial infarction in clinically stable patients with left ventricular dysfunction manifested as an ejection fraction ≤ 40% and to reduce the incidence of overt heart failure and subsequent hospitalizations for congestive heart failure in these patients.

Diabetic Nephropathy: Captopril tablets, USP are indicated for the treatment of diabetic nephropathy (proteinuria > 500 mg/day) in patients with type I insulin-dependent diabetes mellitus and retinopathy. Captopril tablets, USP decreases the rate of progression of renal insufficiency and development of serious adverse clinical outcomes (death or need for renal transplantation or dialysis).

In considering use of captopril tablets, USP, it should be noted that in controlled trials ACE inhibitors have an effect on blood pressure that is less in black patients than in non-blacks. In addition, ACE inhibitors (for which adequate data are available) cause a higher rate of angioedema in black than in non-black patients (see WARNINGS: Head and Neck Angioedema and Intestinal Angioedema).

CONTRAINDICATIONS

Captopril is contraindicated in patients who are hypersensitive to this product or any other angiotensin-converting enzyme inhibitor (e.g., a patient who has experienced angioedema during therapy with any other ACE inhibitor).

Do not co-administer aliskiren with captopril in patients with diabetes (see PRECAUTIONS, Drug Interactions).

Captopril is contraindicated in combination with a neprilysin inhibitor (e.g., sacubitril). Do not administer captopril within 36 hours of switching to or from sacubitril/valsartan, a nepriltsin inhibitor (see PRECAUTIONS, Drug Interactions).

WARNINGS

Anaphylactoid and Possibly Related Reactions

Presumably because angiotensin-converting enzyme inhibitors affect the metabolism of eicosanoids and polypeptides, including endogenous bradykinin, patients receiving ACE inhibitors (including captopril) may be subject to a variety of adverse reactions, some of them serious.

Head and Neck Angioedema: Angioedema involving the extremities, face, lips, mucous membranes, tongue, glottis or larynx has been seen in patients treated with ACE inhibitors, including captopril. If angioedema involves the tongue, glottis or larynx, airway obstruction may occur and be fatal. Emergency therapy, including but not necessarily limited to, subcutaneous administration of a 1:1,000 solution of epinephrine should be promptly instituted.

Swelling confined to the face, mucous membranes of the mouth, lips and extremities has usually resolved with discontinuation of captopril; some cases required medical therapy. (See PRECAUTIONS: Information for Patients and ADVERSE REACTIONS.)

Patients receiving coadministration of ACE inhibitor and mTOR (mammalian target of rapamycin) inhibitor (e.g., temsirolimus, sirolimus, everolimus) therapy or a neprilysin inhibitor may be at increased risk for angioedema (see PRECAUTIONS, Drug Interactions).

Intestinal Angioedema: Intestinal angioedema has been reported in patients treated with ACE inhibitors. These patients presented with abdominal pain (with or without nausea or vomiting); in some cases there was no prior history of facial angioedema and C-1 esterase levels were normal. The angioedema was diagnosed by procedures including abdominal CT scan or ultrasound, or at surgery, and symptoms resolved after stopping the ACE inhibitor. Intestinal angioedema should be included in the differential diagnosis of patients on ACE inhibitors presenting with abdominal pain.

Anaphylactoid reactions during desensitization: Two patients undergoing desensitizing treatment with hymenoptera venom while receiving ACE inhibitors sustained life-threatening anaphylactoid reactions. In the same patients, these reactions were avoided when ACE inhibitors were temporarily withheld, but they reappeared upon inadvertent rechallenge.

Anaphylactoid reactions during membrane exposure: Anaphylactoid reactions have been reported in patients dialyzed with high-flux membranes and treated concomitantly with an ACE inhibitor. Anaphylactoid reactions have also been reported in patients undergoing low-density lipoprotein apheresis with dextran sulfate absorption.

Neutropenia/Agranulocytosis

Neutropenia (< 1,000/mm^3) with myeloid hypoplasia has resulted from use of captopril. About half of the neutropenic patients developed systemic or oral cavity infections or other features of the syndrome of agranulocytosis.

The risk of neutropenia is dependent on the clinical status of the patient:

In clinical trials in patients with hypertension who have normal renal function (serum creatinine less than 1.6 mg/dL and no collagen vascular disease), neutropenia has been seen in one patient out of over 8,600 exposed.

In patients with some degree of renal failure (serum creatinine at least 1.6 mg/dL) but no collagen vascular disease, the risk of neutropenia in clinical trials was about 1 per 500, a frequency over 15 times that for uncomplicated hypertension. Daily doses of captopril were relatively high in these patients, particularly in view of their diminished renal function. In foreign marketing experience in patients with renal failure, use of allopurinol concomitantly with captopril has been associated with neutropenia but this association has not appeared in U.S. reports.

In patients with collagen vascular diseases (e.g., systemic lupus erythematosus, scleroderma) and impaired renal function, neutropenia occurred in 3.7 percent of patients in clinical trials.

While none of the over 750 patients in formal clinical trials of heart failure developed neutropenia, it has occurred during the subsequent clinical experience. About half of the reported cases had serum creatinine ≥ 1.6 mg/dL and more than 75 percent were in patients also receiving procainamide. In heart failure, it appears that the same risk factors for neutropenia are present.

The neutropenia has usually been detected within three months after captopril was started. Bone marrow examinations in patients with neutropenia consistently showed myeloid hypoplasia, frequently accompanied by erythroid hypoplasia and decreased numbers of megakaryocytes (e.g., hypoplastic bone marrow and pancytopenia); anemia and thrombocytopenia were sometimes seen.

In general, neutrophils returned to normal in about two weeks after captopril was discontinued, and serious infections were limited to clinically complex patients. About 13 percent of the cases of neutropenia have ended fatally, but almost all fatalities were in patients with serious illness, having collagen vascular disease, renal failure, heart failure or immunosuppressant therapy, or a combination of these complicating factors.

Evaluation of the hypertensive or heart failure patient should always include assessment of renal function.

If captopril is used in patients with impaired renal function, white blood cell and differential counts should be evaluated prior to starting treatment and at approximately two-week intervals for about three months, then periodically.

In patients with collagen vascular disease or who are exposed to other drugs known to affect the white cells or immune response, particularly when there is impaired renal function, captopril should be used only after an assessment of benefit and risk, and then with caution.

All patients treated with captopril should be told to report any signs of infection (e.g., sore throat, fever). If infection is suspected, white cell counts should be performed without delay.

Since discontinuation of captopril and other drugs has generally led to prompt return of the white count to normal, upon confirmation of neutropenia (neutrophil count < 1,000/mm^3) the physician should withdraw captopril and closely follow the patient’s course.

Proteinuria

Total urinary proteins greater than 1 g per day were seen in about 0.7 percent of patients receiving captopril. About 90 percent of affected patients had evidence of prior renal disease or received relatively high doses of captopril (in excess of 150 mg/day), or both. The nephrotic syndrome occurred in about one-fifth of proteinuric patients. In most cases, proteinuria subsided or cleared within six months whether or not captopril was continued. Parameters of renal function, such as BUN and creatinine, were seldom altered in the patients with proteinuria.

Hypotension

Excessive hypotension was rarely seen in hypertensive patients but is a possible consequence of captopril use in salt/volume depleted persons (such as those treated vigorously with diuretics), patients with heart failure or those patients undergoing renal dialysis. (See PRECAUTIONS: Drug Interactions.)

In heart failure, where the blood pressure was either normal or low, transient decreases in mean blood pressure greater than 20 percent were recorded in about half of the patients. This transient hypotension is more likely to occur after any of the first several doses and is usually well tolerated, producing either no symptoms or brief mild lightheadedness, although in rare instances it has been associated with arrhythmia or conduction defects. Hypotension was the reason for discontinuation of drug in 3.6 percent of patients with heart failure.

BECAUSE OF THE POTENTIAL FALL IN BLOOD PRESSURE IN THESE PATIENTS, THERAPY SHOULD BE STARTED UNDER VERY CLOSE MEDICAL SUPERVISION. A starting dose of 6.25 mg or 12.5 mg three times a day may minimize the hypotensive effect. Patients should be followed closely for the first two weeks of treatment and whenever the dose of captopril and/or diuretic is increased. In patients with heart failure, reducing the dose of diuretic, if feasible, may minimize the fall in blood pressure.

Hypotension is not per se a reason to discontinue captopril. Some decrease of systemic blood pressure is a common and desirable observation upon initiation of captopril tablets, USP treatment in heart failure. The magnitude of the decrease is greatest early in the course of treatment; this effect stabilizes within a week or two, and generally returns to pretreatment levels, without a decrease in therapeutic efficacy, within two months.

Fetal Toxicity

Pregnancy Category D

Use of drugs that act on the renin-angiotensin system during the second and third trimesters of pregnancy reduces fetal renal function and increases fetal and neonatal morbidity and death. Resulting oligohydramnios can be associated with fetal lung hypoplasia and skeletal deformations. Potential neonatal adverse effects include skull hypoplasia, anuria, hypotension, renal failure, and death. When pregnancy is detected, discontinue captopril as soon as possible. These adverse outcomes are usually associated with use of these drugs in the second and third trimester of pregnancy. Most epidemiologic studies examining fetal abnormalities after exposure to antihypertensive use in the first trimester have not distinguished drugs affecting the renin-angiotensin system from other antihypertensive agents. Appropriate management of maternal hypertension during pregnancy is important to optimize outcomes for both mothers and fetus.

In the unusual case that there is no appropriate alternative to therapy with drugs affecting the renin-angiotensin system for a particular patient, apprise the mother of the potential risk to the fetus. Perform serial ultrasound examinations to assess the intra-amniotic environment. If oligohydramnios is observed, discontinue captopril, unless it is considered lifesaving for the mother. Fetal testing may be appropriate, based on the week of pregnancy. Patients and physicians should be aware, however, that oligohydramnios may not appear until after the fetus has sustained irreversible injury. Closely observe infants with histories of in utero exposure to captopril for hypotension, oliguria, and hyperkalemia. [See PRECAUTIONS, Pediatric Use].

When captopril was given to rabbits at doses about 0.8 times to 70 times (on a mg/kg basis) the maximum recommended human dose, low incidences of craniofacial malformations were seen. No teratogenic effects of captopril were seen in studies of pregnant rats and hamsters. On a mg/kg basis, the doses used were up to 150 times (in hamsters) and 625 times (in rats) the maximum recommended human dose.

Hepatic Failure

Rarely, ACE inhibitors have been associated with a syndrome that starts with cholestatic jaundice and progresses to fulminant hepatic necrosis and (sometimes) death. The mechanism of this syndrome is not understood. Patients receiving ACE inhibitors who develop jaundice or marked elevations of hepatic enzymes should discontinue the ACE inhibitor and receive appropriate medical follow-up.

PRECAUTIONS

General

Impaired Renal Function

Hypertension—Some patients with renal disease, particularly those with severe renal artery stenosis, have developed increases in BUN and serum creatinine after reduction of blood pressure with captopril. Captopril dosage reduction and/or discontinuation of diuretic may be required. For some of these patients, it may not be possible to normalize blood pressure and maintain adequate renal perfusion.

Heart Failure—About 20 percent of patients develop stable elevations of BUN and serum creatinine greater than 20 percent above normal or baseline upon long-term treatment with captopril. Less than 5 percent of patients, generally those with severe preexisting renal disease, required discontinuation of treatment due to progressively increasing creatinine; subsequent improvement probably depends upon the severity of the underlying renal disease.

See CLINICAL PHARMACOLOGY, DOSAGE AND ADMINISTRATION, ADVERSE REACTIONS: Altered Laboratory Findings.

Hyperkalemia: Elevations in serum potassium have been observed in some patients treated with ACE inhibitors, including captopril. When treated with ACE inhibitors, patients at risk for the development of hyperkalemia include those with: renal insufficiency; diabetes mellitus; and those using concomitant potassium-sparing diuretics, potassium supplements or potassium-containing salt substitutes; or other drugs associated with increases in serum potassium in a trial of type I diabetic patients with proteinuria, the incidence of withdrawal of treatment with captopril for hyperkalemia was 2% (4/207). In two trials of normotensive type I diabetic patients with microalbuminuria, no captopril group subjects had hyperkalemia (0/116). (See PRECAUTIONS: Information for Patients and Drug Interactions; ADVERSE REACTIONS: Altered Laboratory Findings.)

Cough: Presumably due to the inhibition of the degradation of endogenous bradykinin, persistent nonproductive cough has been reported with all ACE inhibitors, always resolving after discontinuation of therapy. ACE inhibitor-induced cough should be considered in the differential diagnosis of cough.

Valvular Stenosis: There is concern, on theoretical grounds, that patients with aortic stenosis might be at particular risk of decreased coronary perfusion when treated with vasodilators because they do not develop as much afterload reduction as others.

Surgery/Anesthesia: In patients undergoing major surgery or during anesthesia with agents that produce hypotension, captopril will block angiotensin II formation secondary to compensatory renin release. If hypotension occurs and is considered to be due to this mechanism, it can be corrected by volume expansion.

Hemodialysis

Recent clinical observations have shown an association of hypersensitivity-like (anaphylactoid) reactions during hemodialysis with high-flux dialysis membranes (e.g., AN69) in patients receiving ACE inhibitors. In these patients, consideration should be given to using a different type of dialysis membrane or a different class of medication. (See WARNINGS: Anaphylactoid reactions during membrane exposure.)

Information for Patients

Patients should be advised to immediately report to their physician any signs or symptoms suggesting angioedema (e.g., swelling of face, eyes, lips, tongue, larynx and extremities; difficulty in swallowing or breathing; hoarseness) and to discontinue therapy. (See WARNINGS: Head and Neck Angioedema and Intestinal Angioedema.)

Patients should be told to report promptly any indication of infection (e.g., sore throat, fever), which may be a sign of neutropenia, or of progressive edema which might be related to proteinuria and nephrotic syndrome.

All patients should be cautioned that excessive perspiration and dehydration may lead to an excessive fall in blood pressure because of reduction in fluid volume. Other causes of volume depletion such as vomiting or diarrhea may also lead to a fall in blood pressure; patients should be advised to consult with the physician.

Patients should be advised not to use potassium-sparing diuretics, potassium supplements or potassium-containing salt substitutes without consulting their physician. (See PRECAUTIONS: General and Drug Interactions; ADVERSE REACTIONS.)

Patients should be warned against interruption or discontinuation of medication unless instructed by the physician.

Heart failure patients on captopril therapy should be cautioned against rapid increases in physical activity.

Patients should be informed that captopril tablets should be taken one hour before meals (see DOSAGE AND ADMINISTRATION).

Pregnancy: Female patients of childbearing age should be told about the consequences of exposure to captopril tablets during pregnancy. Discuss treatment options with women planning to become pregnant. Patients should be asked to report pregnancies to their physicians as soon as possible.

Drug Interactions

Dual Blockade of the Renin-Angiotensin System (RAS)

Dual blockade of the RAS with angiotensin receptor blockers, ACE inhibitors, or aliskiren is associated with increased risks of hypotension, hyperkalemia, and changes in renal function (including acute renal failure) compared to monotherapy. Most patients receiving the combination of two RAS inhibitors do not obtain any additional benefit compared to monotherapy. In general, avoid combined use of RAS inhibitors. Closely monitor blood pressure, renal function and electrolytes in patients on captopril and other agents that block the RAS.

Do not coadminister aliskiren with captopril in patients with diabetes. Avoid use of aliskiren with captopril in patients with renal impairment (GFR < 60 ml/min).

Non-Steroidal Anti-Inflammatory Agents including Selective Cyclooxygenase – 2 Inhibitors (COX-2 Inhibitors)

In patients who are elderly, volume-depleted (including those on diuretic therapy), or with compromised renal function, coadministration of NSAIDs, including selective COX-2 inhibitors, with ACE inhibitors, including captopril, may result in deterioration of renal function, including possible acute renal failure. These effects are usually reversible. Monitor renal function periodically in patients receiving captopril and NSAID therapy. The antihypertensive effect of ACE inhibitors, including captopril, may be attenuated by NSAIDs.

Hypotension—Patients on Diuretic Therapy: Patients on diuretics and especially those in whom diuretic therapy was recently instituted, as well as those on severe dietary salt restriction or dialysis, may occasionally experience a precipitous reduction of blood pressure usually within the first hour after receiving the initial dose of captopril.

The possibility of hypotensive effects with captopril can be minimized by either discontinuing the diuretic or increasing the salt intake approximately one week prior to initiation of treatment with captopril tablets, USP or initiating therapy with small doses (6.25 mg or 12.5 mg). Alternatively, provide medical supervision for at least one hour after the initial dose. If hypotension occurs, the patient should be placed in a supine position and, if necessary, receive an intravenous infusion of normal saline. This transient hypotensive response is not a contraindication to further doses which can be given without difficulty once the blood pressure has increased after volume expansion.

Agents Having Vasodilator Activity: Data on the effect of concomitant use of other vasodilators in patients receiving captopril for heart failure are not available; therefore, nitroglycerin or other nitrates (as used for management of angina) or other drugs having vasodilator activity should, if possible, be discontinued before starting captopril tablets. If resumed during captopril tablets therapy, such agents should be administered cautiously, and perhaps at lower dosage.

Agents Causing Renin Release: Captopril’s effect will be augmented by antihypertensive agents that cause renin release. For example, diuretics (e.g., thiazides) may activate the renin-angiotensin-aldosterone system.

Agents Affecting Sympathetic Activity: The sympathetic nervous system may be especially important in supporting blood pressure in patients receiving captopril alone or with diuretics. Therefore, agents affecting sympathetic activity (e.g., ganglionic blocking agents or adrenergic neuron blocking agents) should be used with caution. Beta-adrenergic blocking drugs add some further antihypertensive effect to captopril, but the overall response is less than additive.

Agents Increasing Serum Potassium: Since captopril decreases aldosterone production, elevation of serum potassium may occur. Potassium-sparing diuretics such as spironolactone, triamterene, or amiloride, or potassium supplements should be given only for documented hypokalemia, and then with caution, since they may lead to a significant increase of serum potassium. Salt substitutes containing potassium should also be used with caution.

Lithium: Increased serum lithium levels and symptoms of lithium toxicity have been reported in patients receiving concomitant lithium and ACE inhibitor therapy. These drugs should be coadministered with caution and frequent monitoring of serum lithium levels is recommended. If a diuretic is also used, it may increase the risk of lithium toxicity.

Cardiac Glycosides: In a study of young healthy male subjects no evidence of a direct pharmacokinetic captopril-digoxin interaction could be found.

Loop Diuretics: Furosemide administered concurrently with captopril does not alter the pharmacokinetics of captopril in renally impaired hypertensive patients.

Allopurinol: In a study of healthy male volunteers no significant pharmacokinetic interaction occurred when captopril and allopurinol were administered concomitantly for 6 days.

Neprilysin Inhibitor: Patients taking concomitant neprilysin inhibitors may be at increased risk for angioedema. (See WARNINGS, Head and Neck Angioedema).

Gold: Nitritoid reactions (symptoms include facial flushing, nausea, vomiting and hypotension) have been reported rarely in patients on therapy with injectable gold (sodium aurothiomalate) and concomitant ACE inhibitor therapy including captopril.

Drug/Laboratory Test Interaction

Captopril may cause a false-positive urine test for acetone.

Carcinogenesis, Mutagenesis, Impairment of Fertility

Two-year studies with doses of 50 mg/kg/day to 1,350 mg/kg/day in mice and rats failed to show any evidence of carcinogenic potential. The high dose in these studies is 150 times the maximum recommended human dose of 450 mg, assuming a 50 kg subject. On a body-surface-area basis, the high doses for mice and rats are 13 times and 26 times the maximum recommended human dose, respectively.

Studies in rats have revealed no impairment of fertility.

Animal Toxicology

Chronic oral toxicity studies were conducted in rats (2 years), dogs (47 weeks; 1 year), mice (2 years), and monkeys (1 year). Significant drug-related toxicity included effects on hematopoiesis, renal toxicity, erosion/ulceration of the stomach, and variation of retinal blood vessels.

Reductions in hemoglobin and/or hematocrit values were seen in mice, rats, and monkeys at doses 50 times to 150 times the maximum recommended human dose (MRHD) of 450 mg, assuming a 50 kg subject. On a body-surface-area basis, these doses are 5 times to 25 times maximum recommended dose (MRHD). Anemia, leukopenia, thrombocytopenia, and bone marrow suppression occurred in dogs at doses 8 times to 30 times MRHD on a body-weight basis (4 times to 15 times MRHD on a surface-area basis). The reductions in hemoglobin and hematocrit values in rats and mice were only significant at 1 year and returned to normal with continued dosing by the end of the study. Marked anemia was seen at all dose levels (8 times to 30 times MRHD) in dogs, whereas moderate to marked leukopenia was noted only at 15 times and 30 times MRHD and thrombocytopenia at 30 times MRHD. The anemia could be reversed upon discontinuation of dosing. Bone marrow suppression occurred to a varying degree, being associated only with dogs that died or were sacrificed in a moribund condition in the 1 year study. However, in the 47 week study at a dose 30 times MRHD, bone marrow suppression was found to be reversible upon continued drug administration.

Captopril caused hyperplasia of the juxtaglomerular apparatus of the kidneys in mice and rats at doses 7 times to 200 times MRHD on a body-weight basis (0.6 times to 35 times MRHD on a surface-area basis); in monkeys at 20 times to 60 times MRHD on a body-weight basis (7 times to 20 times MRHD on a surface-area basis); and in dogs at 30 times MRHD on a body-weight basis (15 times MRHD on a surface-area basis).

Gastric erosions/ulcerations were increased in incidence in male rats at 20 times to 200 times MRHD on a body-weight basis (3.5 times and 35 times MRHD on a surface-area basis); in dogs at 30 times MRHD on a body-weight basis (15 times on MRHD on a surface-area basis); and in monkeys at 65 times MRHD on a body-weight basis (20 times MRHD on a surface-area basis). Rabbits developed gastric and intestinal ulcers when given oral doses approximately 30 times MRHD on a body-weight basis (10 times MRHD on surface-area basis) for only 5 days to 7 days.

In the two-year rat study, irreversible and progressive variations in the caliber of retinal vessels (focal sacculations and constrictions) occurred at all dose levels (7 times to 200 times MRHD) on a body-weight basis; 1 time to 35 times MRHD on a surface-area basis in a dose-related fashion. The effect was first observed in the 88th week of dosing, with a progressively increased incidence thereafter, even after cessation of dosing.

Nursing Mothers

Concentrations of captopril in human milk are approximately one percent of those in maternal blood. Because of the potential for serious adverse reactions in nursing infants from captopril, a decision should be made whether to discontinue nursing or to discontinue the drug, taking into account the importance of captopril to the mother. (See PRECAUTIONS: Pediatric Use.)

Pediatric Use

Neonates with a history of in utero exposure to captopril:

If oliguria or hypotension occurs, direct attention toward support of blood pressure and renal perfusion. Exchange transfusions or dialysis may be required as a means of reversing hypotension and/or substituting for disordered renal function. While captopril may be removed from the adult circulation by hemodialysis, there is inadequate data concerning the effectiveness of hemodialysis for removing it from the circulation of neonates or children. Peritoneal dialysis is not effective for removing captopril; there is no information concerning exchange transfusion for removing captopril form the general circulation.

Safety and effectiveness in pediatric patients have not been established. There is limited experience reported in the literature with the use of captopril in the pediatric population; dosage, on a weight basis, was generally reported to be comparable to or less than that used in adults.

Infants, especially newborns, may be more susceptible to the adverse hemodynamic effects of captopril. Excessive, prolonged and unpredictable decreases in blood pressure and associated complications, including oliguria and seizures, have been reported.

Captopril should be used in pediatric patients only if other measures for controlling blood pressure have not been effective.

ADVERSE REACTIONS

Reported incidences are based on clinical trials involving approximately 7,000 patients.

Renal: About one of 100 patients developed proteinuria (see WARNINGS).

Each of the following has been reported in approximately 1 to 2 of 1,000 patients and are of uncertain relationship to drug use: renal insufficiency, renal failure, nephrotic syndrome, polyuria, oliguria, and urinary frequency.

Hematologic: Neutropenia/agranulocytosis has occurred (see WARNINGS). Cases of anemia, thrombocytopenia, and pancytopenia have been reported.

Dermatologic: Rash, often with pruritus, and sometimes with fever, arthralgia, and eosinophilia, occurred in about 4 to 7 (depending on renal status and dose) of 100 patients, usually during the first four weeks of therapy. It is usually maculopapular, and rarely urticarial. The rash is usually mild and disappears within a few days of dosage reduction, short-term treatment with an antihistaminic agent, and/or discontinuing therapy; remission may occur even if captopril is continued. Pruritus, without rash, occurs in about 2 of 100 patients. Between 7 percent and 10 percent of patients with skin rash have shown an eosinophilia and/or positive ANA titers. A reversible associated pemphigoid-like lesion, and photosensitivity, have also been reported.

Flushing or pallor has been reported in 2 to 5 of 1,000 patients.

Cardiovascular: Hypotension may occur; see WARNINGS and PRECAUTIONS [Drug Interactions] for discussion of hypotension with captopril therapy.

Tachycardia, chest pain, and palpitations have each been observed in approximately 1 of 100 patients.

Angina pectoris, myocardial infarction, Raynaud’s syndrome, and congestive heart failure have each occurred in 2 to 3 of 1,000 patients.

Dysgeusia: Approximately 2 to 4 (depending on renal status and dose) of 100 patients developed a diminution or loss of taste perception. Taste impairment is reversible and usually self-limited (2 months to 3 months) even with continued drug administration. Weight loss may be associated with the loss of taste.

Angioedema: Angioedema involving the extremities, face, lips, mucous membranes, tongue, glottis or larynx has been reported in approximately one in 1,000 patients. Angioedema involving the upper airways has caused fatal airway obstruction. (See WARNINGS: Head and Neck Angioedema, Intestinal Angioedema and PRECAUTIONS: Information for Patients.)

Cough: Cough has been reported in 0.5% to 2% of patients treated with captopril in clinical trials (see PRECAUTIONS: General, Cough).

The following have been reported in about 0.5 percent to 2 percent of patients but did not appear at increased frequency compared to placebo or other treatments used in controlled trials: gastric irritation, abdominal pain, nausea, vomiting, diarrhea, anorexia, constipation, aphthous ulcers, peptic ulcer, dizziness, headache, malaise, fatigue, insomnia, dry mouth, dyspnea, alopecia, paresthesias.

Other clinical adverse effects reported since the drug was marketed are listed below by body system. In this setting, an incidence or causal relationship cannot be accurately determined.

Body as a whole: Anaphylactoid reactions (see WARNINGS: Anaphylactoid and possible related reactions and PRECAUTIONS: Hemodialysis).

General: Asthenia, gynecomastia.

Cardiovascular: Cardiac arrest, cerebrovascular accident/insufficiency, rhythm disturbances, orthostatic hypotension, syncope.

Dermatologic: Bullous pemphigus, erythema multiforme (including Stevens-Johnson syndrome), exfoliative dermatitis.

Gastrointestinal: Pancreatitis, glossitis, dyspepsia.

Hematologic: Anemia, including aplastic and hemolytic.

Hepatobiliary: Jaundice, hepatitis, including rare cases of necrosis, cholestasis.

Metabolic: Symptomatic hyponatremia.

Musculoskeletal: Myalgia, myasthenia.

Nervous/Psychiatric: Ataxia, confusion, depression, nervousness, somnolence.

Respiratory: Bronchospasm, eosinophilic pneumonitis, rhinitis.

Special Senses: Blurred vision.

Urogenital: Impotence.

As with other ACE inhibitors, a syndrome has been reported which may include: fever, myalgia, arthralgia, interstitial nephritis, vasculitis, rash or other dermatologic manifestations, eosinophilia and an elevated ESR.

Altered Laboratory Findings

Serum Electrolytes: Hyperkalemia: small increases in serum potassium, especially in patients with renal impairment (see PRECAUTIONS).

Hyponatremia: particularly in patients receiving a low sodium diet or concomitant diuretics.

BUN/Serum Creatinine: Transient elevations of BUN or serum creatinine especially in volume or salt depleted patients or those with renovascular hypertension may occur. Rapid reduction of longstanding or markedly elevated blood pressure can result in decreases in the glomerular filtration rate and, in turn, lead to increases in BUN or serum creatinine.

Hematologic: A positive ANA has been reported.

Liver Function Tests: Elevations of liver transaminases, alkaline phosphatase, and serum bilirubin have occurred.

OVERDOSAGE

Correction of hypotension would be of primary concern. Volume expansion with an intravenous infusion of normal saline is the treatment of choice for restoration of blood pressure.

While captopril may be removed from the adult circulation by hemodialysis, there is inadequate data concerning the effectiveness of hemodialysis for removing it from the circulation of neonates or children. Peritoneal dialysis is not effective for removing captopril; there is no information concerning exchange transfusion for removing captopril from the general circulation.

DOSAGE AND ADMINISTRATION

Captopril tablets, USP should be taken one hour before meals. Dosage must be individualized.

Hypertension: Initiation of therapy requires consideration of recent antihypertensive drug treatment, the extent of blood pressure elevation, salt restriction, and other clinical circumstances. If possible, discontinue the patient’s previous antihypertensive drug regimen for one week before starting captopril.

The initial dose of captopril tablets, USP is 25 mg twice daily or three times a day. If satisfactory reduction of blood pressure has not been achieved after one week or two weeks, the dose may be increased to 50 mg twice daily or three times a day. Concomitant sodium restriction may be beneficial when captopril is used alone.

The dose of captopril tablets, USP in hypertension usually does not exceed 50 mg three times a day. Therefore, if the blood pressure has not been satisfactorily controlled after one week to two weeks at this dose, (and the patient is not already receiving a diuretic), a modest dose of a thiazide-type diuretic (e.g., hydrochlorothiazide, 25 mg daily), should be added. The diuretic dose may be increased at one-week to two-week intervals until its highest usual antihypertensive dose is reached.

If captopril is being started in a patient already receiving a diuretic, captopril therapy should be initiated under close medical supervision (see WARNINGS and PRECAUTIONS: Drug Interactions regarding hypotension), with dosage and titration of captopril as noted above.

If further blood pressure reduction is required, the dose of captopril tablets, USP may be increased to 100 mg twice daily or three times a day and then, if necessary, to 150 mg twice daily or three times a day (while continuing the diuretic). The usual dose range is 25 mg to 150 mg twice daily or three times a day. A maximum daily dose of 450 mg captopril tablets, USP should not be exceeded.

For patients with severe hypertension (e.g., accelerated or malignant hypertension), when temporary discontinuation of current antihypertensive therapy is not practical or desirable, or when prompt titration to more normotensive blood pressure levels is indicated, diuretic should be continued but other current antihypertensive medication stopped and captopril tablets, USP dosage promptly initiated at 25 mg twice daily or three times a day, under close medical supervision.

When necessitated by the patient’s clinical condition, the daily dose of captopril tablets, USP may be increased every 24 hours or less under continuous medical supervision until a satisfactory blood pressure response is obtained or the maximum dose of captopril is reached. In this regimen, addition of a more potent diuretic, e.g., furosemide, may also be indicated.

Beta-blockers may also be used in conjunction with captopril therapy (see PRECAUTIONS: Drug Interactions), but the effects of the two drugs are less than additive.

Heart Failure: Initiation of therapy requires consideration of recent diuretic therapy and the possibility of severe salt/volume depletion. In patients with either normal or low blood pressure, who have been vigorously treated with diuretics and who may be hyponatremic and/or hypovolemic, a starting dose of 6.25 mg or 12.5 mg three times a day may minimize the magnitude or duration of the hypotensive effect (see WARNINGS: Hypotension); for these patients, titration to the usual daily dosage can then occur within the next several days.

For most patients the usual initial daily dosage is 25 mg three times a day. After a dose of 50 mg three times a day is reached, further increases in dosage should be delayed, where possible, for at least two weeks to determine if a satisfactory response occurs. Most patients studied have had a satisfactory clinical improvement at 50 mg or 100 mg three times a day. A maximum daily dose of 450 mg of captopril tablets should not be exceeded.

Captopril should generally be used in conjunction with a diuretic and digitalis. Captopril therapy must be initiated under very close medical supervision.

Left Ventricular Dysfunction After Myocardial Infarction: The recommended dose for long-term use in patients following a myocardial infarction is a target maintenance dose of 50 mg three times a day.

Therapy may be initiated as early as three days following a myocardial infarction. After a single dose of 6.25 mg, captopril therapy should be initiated at 12.5 mg three times a day. Captopril tablets, USP should then be increased to 25 mg three times a day during the next several days and to a target dose of 50 mg three times a day over the next several weeks as tolerated (see CLINICAL PHARMACOLOGY).

Captopril may be used in patients treated with other post-myocardial infarction therapies, e.g., thrombolytics, aspirin, beta blockers.

Diabetic Nephropathy: The recommended dose of captopril tablets, USP for long term use to treat diabetic nephropathy is 25 mg three times a day.

Other antihypertensives such as diuretics, beta blockers, centrally acting agents or vasodilators may be used in conjunction with captopril if additional therapy is required to further lower blood pressure.

Dosage Adjustment in Renal Impairment: Because captopril is excreted primarily by the kidneys, excretion rates are reduced in patients with impaired renal function. These patients will take longer to reach steady-state captopril levels and will reach higher steady-state levels for a given daily dose than patients with normal renal function. Therefore, these patients may respond to smaller or less frequent doses.

Accordingly, for patients with significant renal impairment, initial daily dosage of captopril should be reduced, and smaller increments utilized for titration, which should be quite slow (one-week to two-week intervals). After the desired therapeutic effect has been achieved, the dose should be slowly back-titrated to determine the minimal effective dose. When concomitant diuretic therapy is required, a loop diuretic (e.g., furosemide), rather than a thiazide diuretic, is preferred in patients with severe renal impairment. (See WARNINGS: Anaphylactoid reactions during membrane exposure and PRECAUTIONS: Hemodialysis.)

HOW SUPPLIED

Captopril tablets, USP are available containing 12.5 mg, 25 mg, 50 mg or 100 mg of captopril, USP.

The 12.5 mg tablets are white to off-white, oval shaped, flat beveled edged uncoated tablets having break line on both sides and one side debossed with “C” on one side of the break line and “1” on other side of the break line (bisect). They are available as follows:

Cartons of 100 tablets (10 tablets each blister pack x 10), NDC 0904-7105-61

The 25 mg tablets are white to off-white, round, flat beveled edged, uncoated tablets debossed with “2” over “C” one side and quadrisect score on the other side. They are available as follows:

Cartons of 100 tablets (10 tablets each blister pack x 10), NDC 0904-7106-61

WARNING: These Unit Dose packages are not child resistant and are Intended for Institutional Use Only. Keep this and all drugs out of the reach of children.

All captopril tablets, USP are white to off-white and may exhibit a slight sulfurous odor.

Storage

Store at 20°C to 25°C (68°F to 77°F); excursions permitted to 15°C to 30°C (59°F to 86°F) [see USP Controlled Room Temperature]. Keep bottles tightly closed (protect from moisture).

All trademarks are the properties of their respective owners.

Product of Spain

Manufactured by:
Ajanta Pharma Limited, India
Marketed by:
Ajanta Pharma USA Inc.
Bridgewater, NJ 08807.

Packaged and Distributed by:

MAJOR® PHARMACEUTICALS

Indianapolis, IN 46268 USA

Refer to package label for Distributor's NDC Number

Revised: 11/2025

Package/Label Display Panel

MAJOR®

NDC 0904-7105-61

Unit Dose

Captopril

Tablets, USP

12.5 mg

100 TABLETS (10 x 10)

Rx only

Package/Label Display Panel

MAJOR®

NDC 0904-7106-61

Unit Dose

Captopril

Tablets, USP

25 mg

100 TABLETS (10 x 10)

Rx only